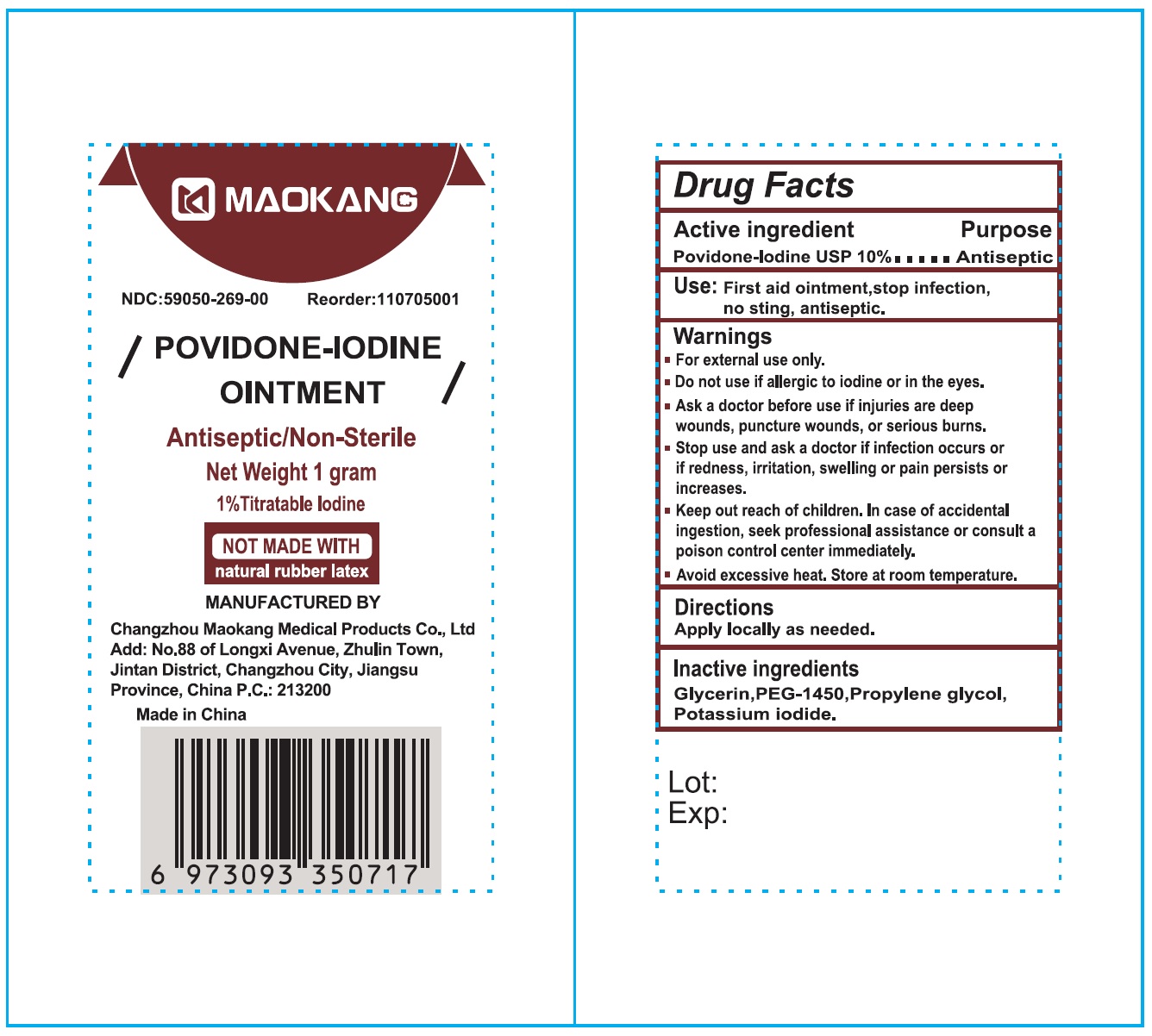 DRUG LABEL: Maokang 10 Povidone Iodine
NDC: 59050-269 | Form: OINTMENT
Manufacturer: Changzhou Maokang Medical Products Co., Ltd
Category: otc | Type: HUMAN OTC DRUG LABEL
Date: 20241121

ACTIVE INGREDIENTS: POVIDONE-IODINE 100 mg/1 g
INACTIVE INGREDIENTS: GLYCERIN; POLYETHYLENE GLYCOL 1450; PROPYLENE GLYCOL; POTASSIUM IODIDE

10% Povidone Iodine Ointment

Active ingredient

Povidone-Iodine USP 10%

Purpose

Antiseptic

Use:

First aid onitment, stop infection, no sting, antiseptic.

Warnings

- For external use only.

Do not use

- if allergic to iodine or in the eyes.

Ask a doctor before use

- if injuries are deep wounds, puncture wounds, or serious burns.

Stop use and ask a doctor if

- infection occurs or redness, irritation, swelling or pain persists or increases.

Keep out of reach of children.

- In case of accidental ingestion, seek professional assistance or consult a Poison Control Center immediately.
- Avoid excessive heat. Store at room temperature.

Directions

apply locally as needed.

Inactive ingredients

Glycerin, PEG-1450, Propylene glycol, Potassium iodide.